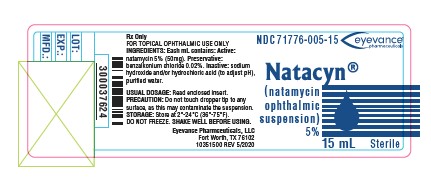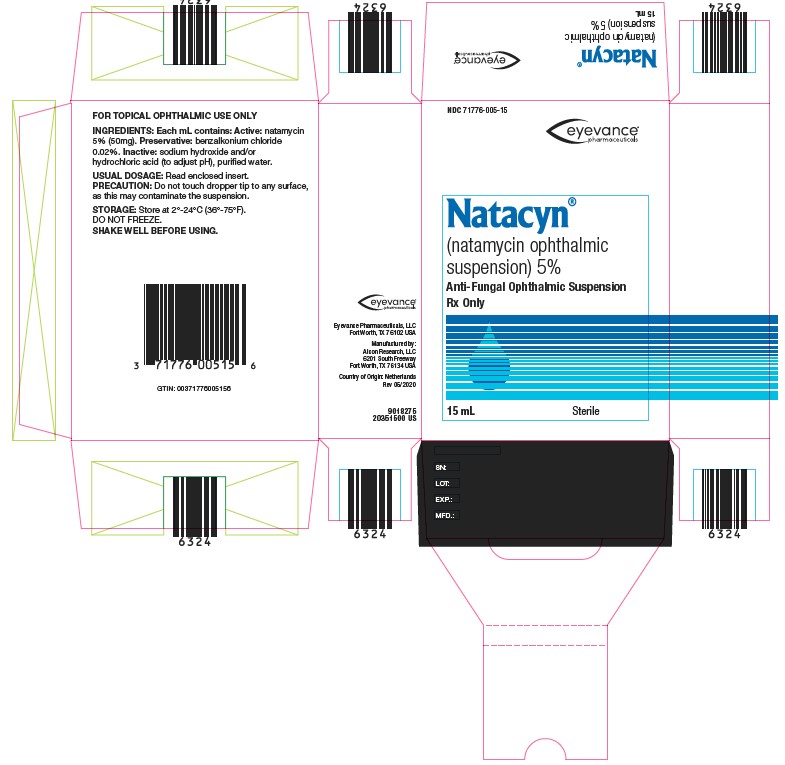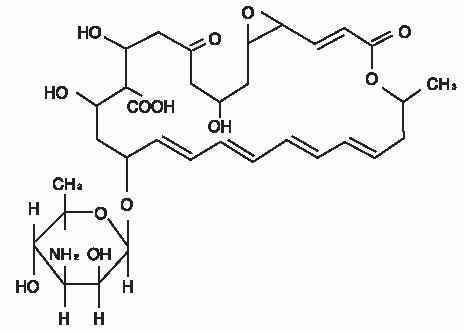 DRUG LABEL: NATACYN
NDC: 71776-005 | Form: SUSPENSION/ DROPS
Manufacturer: Eyevance Pharmaceuticals, LLC
Category: prescription | Type: HUMAN PRESCRIPTION DRUG LABEL
Date: 20251105

ACTIVE INGREDIENTS: NATAMYCIN 50 mg/1 mL
INACTIVE INGREDIENTS: SODIUM HYDROXIDE; HYDROCHLORIC ACID; WATER; BENZALKONIUM CHLORIDE

NATACYN®(natamycin ophthalmic suspension) 5%
Sterile

DESCRIPTION:

NATACYN®(natamycin ophthalmic suspension) 5% is a sterile, antifungal drug for topical ophthalmic administration. Each mL of NATACYN®(natamycin ophthalmic suspension) contains: Active:natamycin 5% (50 mg). Preservative:benzalkonium chloride 0.02%. Inactive:sodium hydroxide and/or hydrochloric acid (neutralized to adjust the pH), purified water.

The active ingredient is represented by the chemical structure:

Established Name:

Natamycin

Molecular Formula:C33H47NO13

Molecular Weight:665.73 g/mol

Chemical Name:Stereoisomer of 22-[(3-amino-3,6-dideoxy- β-D-mannopyranosyl)oxy]-1,3,26- trihydroxy-12- methyl-10-oxo-6,11,28- trioxatricyclo[22.3.1.05,7] octacosa-8,14,16,18,20-pentaene-25- carboxylic acid.

Other:Pimaricin

The pH range is 5.0-7.5.

CLINICAL PHARMACOLOGY:

Natamycin is a tetraene polyene antibiotic derived from Streptomyces natalensis. It possesses in vitroactivity against a variety of yeast and filamentous fungi, including Candida, Aspergillus, Cephalosporium, Fusariumand Penicillium. The mechanism of action appears to be through binding of the molecule to the sterol moiety of the fungal cell membrane. The polyenesterol complex alters the permeability of the membrane to produce depletion of essential cellular constituents. Although the activity against fungi is dose-related, natamycin is predominantly fungicidal. Natamycin is not effective in vitroagainst gram-positive or gram-negative bacteria. Topical administration appears to produce effective concentrations of natamycin within the corneal stroma but not in intraocular fluid. Systemic absorption should not be expected following topical administration of NATACYN®(natamycin ophthalmic suspension) 5%. As with other polyene antibiotics, absorption from the gastrointestinal tract is very poor. Studies in rabbits receiving topical natamycin revealed no measurable compound in the aqueous humor or sera, but the sensitivity of the measurement was no greater than 2 mg/mL.

INDICATIONS AND USAGE:

NATACYN®(natamycin ophthalmic suspension) 5% is indicated for the treatment of fungal blepharitis, conjunctivitis, and keratitis caused by susceptible organisms including Fusarium solanikeratitis. As in other forms of suppurative keratitis, initial and sustained therapy of fungal keratitis should be determined by the clinical diagnosis, laboratory diagnosis by smear and culture of corneal scrapings and drug response. Whenever possible the in vitroactivity of natamycin against the responsible fungus should be determined. The effectiveness of natamycin as a single agent in fungal endophthalmitis has not been established.

CONTRAINDICATIONS:

NATACYN®(natamycin ophthalmic suspension) 5% is contraindicated in individuals with a history of hypersensitivity to any of its components.

PRECAUTIONS: General.

FOR TOPICAL OPHTHALMIC USE ONLY — NOT FOR INJECTION. Failure of improvement of keratitis following 7-10 days of administration of the drug suggests that the infection may be caused by a microorganism not susceptible to natamycin.

Continuation of therapy should be based on clinical re-evaluation and additional laboratory studies.

Adherence of the suspension to areas of epithelial ulceration or retention of the suspension in the fornices occurs regularly. Use only if the container is undamaged.

Information for Patients:

Do not touch dropper tip to any surface, as this may contaminate the suspension. Patients should be advised not to wear contact lenses if they have signs and symptoms of fungal blepharitis, conjunctivitis, and keratitis.

Carcinogenesis, Mutagenesis, Impairment of Fertility:

There have been no long term studies done using natamycin in animals to evaluate carcinogenesis, mutagenesis, or impairment of fertility.

Pregnancy:

Animal reproduction studies have not been conducted with natamycin. It is also not known whether natamycin can cause fetal harm when administered to a pregnant woman or can affect reproduction capacity. NATACYN®(natamycin ophthalmic suspension) 5% should be given to a pregnant woman only if clearly needed.

Nursing Mothers:

It is not known whether these drugs are excreted in human milk. Because many drugs are excreted in human milk, caution should be exercised when natamycin is administered to a nursing woman.

Pediatric Use:

Safety and effectiveness in pediatric patients have not been established.

Geriatric Use:

No overall differences in safety or effectiveness have been observed between elderly and younger patients.

ADVERSE REACTIONS:

The following events have been identified during post-marketing use of NATACYN®(natamycin ophthalmic suspension) 5% in clinical practice. Because they are reported voluntarily from a population of unknown size, estimates of frequency cannot be made. The events, which have been chosen for inclusion due to their seriousness, frequency of reporting, possible causal connection to NATACYN®(natamycin ophthalmic suspension) 5%, or a combination of these factors include: allergic reaction, change in vision, chest pain, corneal opacity, dyspnea, eye discomfort, eye edema, eye hyperemia, eye irritation, eye pain, foreign body sensation, parethesia, and tearing.

DOSAGE AND ADMINISTRATION:

SHAKE WELL BEFORE USING. The preferred initial dosage in fungal keratitis is one drop of NATACYN®(natamycin ophthalmic suspension) 5% instilled in the conjunctival sac at hourly or two-hourly intervals. The frequency of application can usually be reduced to one drop 6 to 8 times daily after the first 3 to 4 days. Therapy should generally be continued for 14 to 21 days or until there is resolution of active fungal keratitis. In many cases, it may be helpful to reduce the dosage gradually at 4 to 7 day intervals to assure that the replicating organism has been eliminated. Less frequent initial dosage (4 to 6 daily applications) may be sufficient in fungal blepharitis and conjunctivitis.

HOW SUPPLIED:

NATACYN®(natamycin ophthalmic suspension) 5% is a 15 mL fill packaged in a 15 mL amber glass bottle with a black closure. A flint glass dropper with a red plastic closure and a black rubber bulb are packaged separately in a clear plastic blister with Tyvek backing.

15 mL NDC71776-005-15

STORAGE:Store between 2°C to 24°C (36°F-75°F). Do not freeze. Avoid exposure to light and excessive heat.

Rx Only

Distributed by:

Eyevance Pharmceuticals, LLC

Fort Worth, Texas 76134

Revised: 05/2020